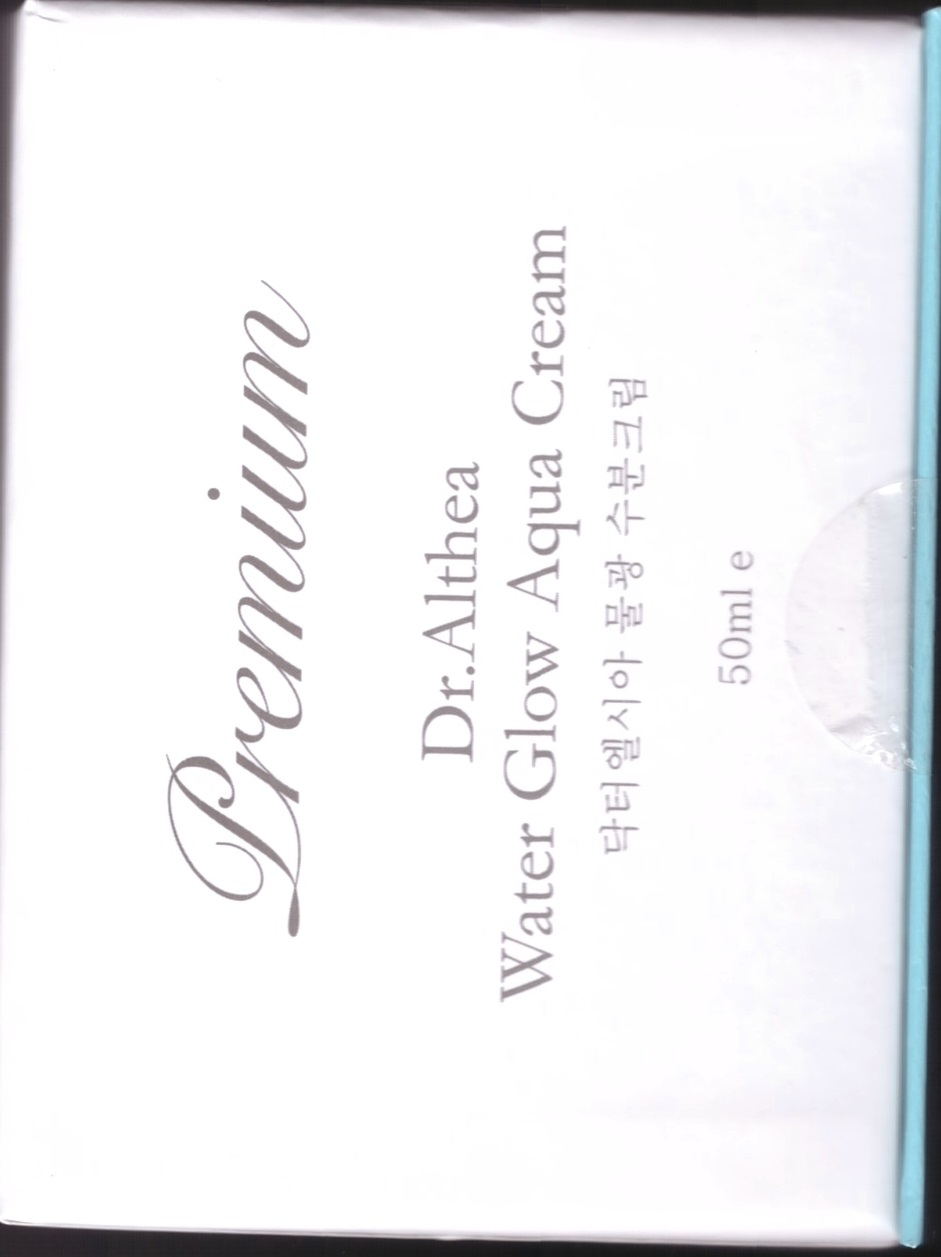 DRUG LABEL: DR.ALTHEA WATER GLOW AQUA
NDC: 70905-0001 | Form: CREAM
Manufacturer: Dr. Althea
Category: otc | Type: HUMAN OTC DRUG LABEL
Date: 20160812

ACTIVE INGREDIENTS: PROPOLIS WAX 0.1 g/100 mL
INACTIVE INGREDIENTS: WATER; BUTYLENE GLYCOL

Drug Facts

ACTIVE INGREDIENT

PROPOLIS EXTRACT

INACTIVE INGREDIENT

WATER, CYCLOPENTASILOXANE, GLYCERIN, ALCOHOL, BETAINE, PEG-32, HYDROGENATED POLY(C6-14 OLEFIN), HYDROGENATED POLYDECENE, XANTHAN GUM, POLYACRYLAMIDE, 1,2-HEXANEDIOL, DIMETHICONOL, HYDROGENATED LECITHIN, PHENOXYETHANOL, PIPER METHYSTICUM LEAF/ROOT/STEM EXTRACT, C13-14 ISOPARAFFIN, BUTYLENE GLYCOL, TROMETHAMINE, PORTULACA OLERACEA EXTRACT, PUERARIA THUNBERGIANA ROOT EXTRACT, CNIDIUM OFFICINALE ROOT EXTRACT, GLYCYRRHIZA GLABRA (LICORICE) ROOT EXTRACT, PAEONIA LACTIFLORA ROOT EXTRACT, ACHILLEA MILLEFOLIUM EXTRACT, ALCHEMILLA VULGARIS EXTRACT, AMARANTHUS CAUDATUS SEED EXTRACT, MALVA SYLVESTRIS (MALLOW) EXTRACT, MELISSA OFFICINALIS LEAF, MENTHA PIPERITA (PEPPERMINT) LEAF EXTRACT, PRIMULA VERIS EXTRACT, ULMUS DAVIDIANA ROOT EXTRACT, VERONICA OFFICINALIS FLOWER/LEAF/STEM EXTRACT, LAURETH-7, ACRYLATES/C10-30 ALKYL ACRYLATE CROSSPOLYMER, CARBOMER, ETHYLHEXYLGLYCERIN, SOLUBLE COLLAGEN, CITRUS AURANTIUM DULCIS (ORANGE) OIL, DISODIUM EDTA, CITRUS LIMON (LEMON) FRUIT OIL, ALOE BARBADENSIS LEAF JUICE, SODIUM HYALURONATE, CITRUS AURANTIUM BERGAMIA (BERGAMOT) FRUIT OIL, CYMBOPOGON SCHOENANTHUS OIL, DIMETHICONE, HYDROGENATED POLYISOBUTENE, SQUALANE, CYMBOPOGON NARDUS (CITRONELLA) OIL, GERANIUM MACULATUM OIL, ARGANIA SPINOSA KERNEL OIL, ISONONYL ISONONANOATE, POLYGLYCERYL-10 STEARATE, BUTYROSPERMUM PARKII (SHEA) BUTTER, CETEARYL ALCOHOL, POLYGLYCERYL-2 DIPOLYHYDROXYSTEARATE, STEARIC ACID SURFACTANT, INULIN LAURYL CARBAMATE, DISODIUM STEAROYL GLUTAMATE

PURPOSE

helps hydrate skin

keep out of reach of the children

INDICATIONS AND USAGE

After washing face in the morning and evening, apply at the last step of skin care

WARNINGS

1. If the following symptoms occur after product use, stop using the product immediately and consult a dermatologist (continuous use can exacerbate the symptoms).
1) Occurrence of red spots, swelling, itchiness, and other skin irritation
2) If the symptoms above occur after the application area is exposed to direct sunlight
2. Do not use on open wounds, eczema, and other skin irritations
3. Precaution for Storage and Handling
1) Close the lid after use
2) Keep out of reach of infants and children
3) Do not to store in a place with high/low temperature and exposed to direct sunlight

DOSAGE AND ADMINISTRATION

for external use only